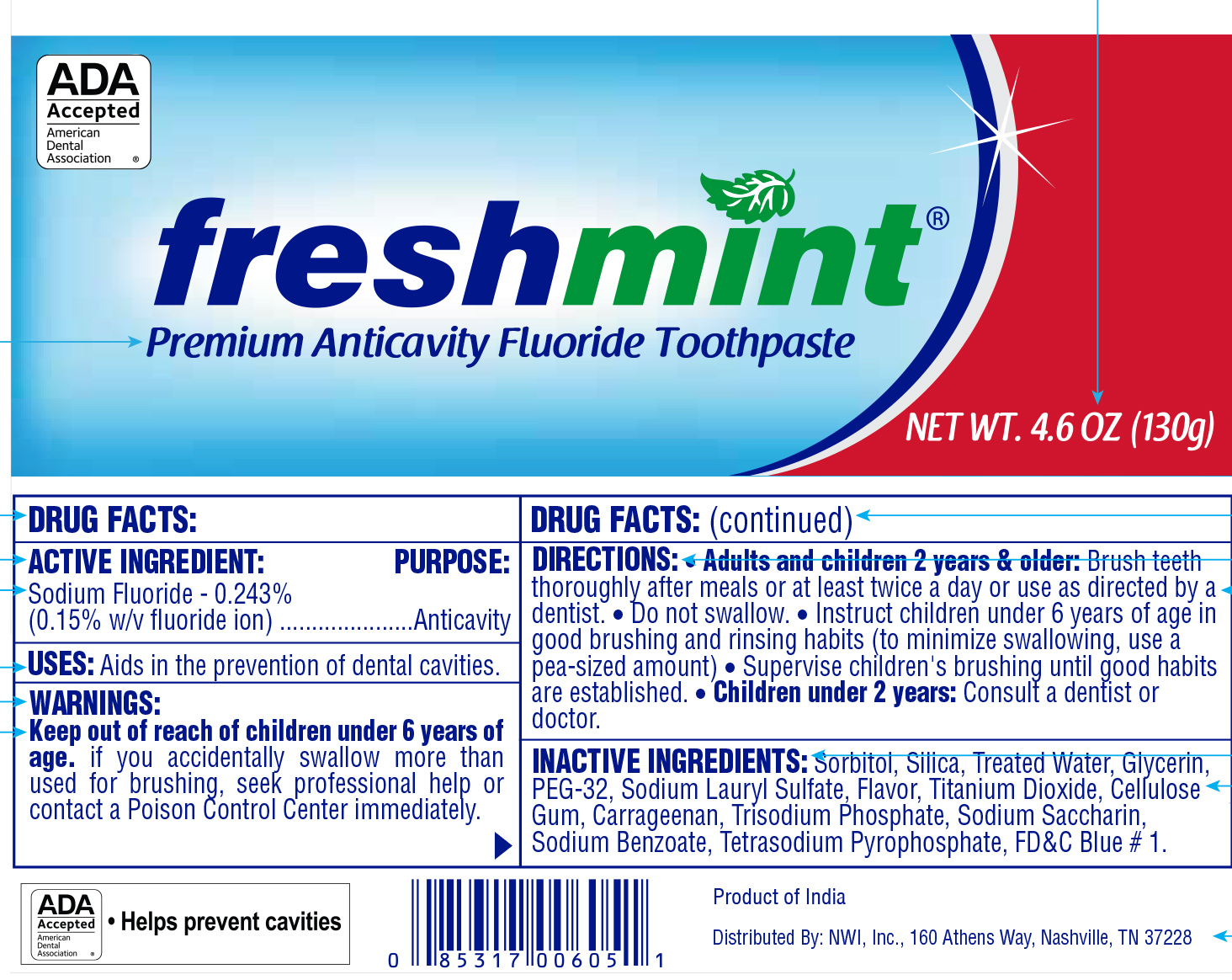 DRUG LABEL: Freshmint Premium Anticavity
NDC: 51824-034 | Form: PASTE, DENTIFRICE
Manufacturer: New World Imports, Inc
Category: otc | Type: HUMAN OTC DRUG LABEL
Date: 20251202

ACTIVE INGREDIENTS: SODIUM FLUORIDE 2.43 mg/1 g
INACTIVE INGREDIENTS: SORBITOL; SILICON DIOXIDE; WATER; GLYCERIN; POLYETHYLENE GLYCOL 1600; SODIUM LAURYL SULFATE; TITANIUM DIOXIDE; CARBOXYMETHYLCELLULOSE SODIUM, UNSPECIFIED; CARRAGEENAN; SODIUM PHOSPHATE, TRIBASIC, DODECAHYDRATE; SODIUM SACCHARIN; SODIUM BENZOATE; SODIUM PYROPHOSPHATE; FD&C BLUE NO. 1

OTC Active Ingredient

Sodium Fluoride - 0.243% (0.15 w/v fluoride ion)

OTC Purpose

Anticavity

Keep out of reach of Children under 6 years of age

If you accidentally swallow more than used for brushing, seek professional help or contact a Poison Control Center immediately.

Uses

Aids in the prevention of dental cavities

Warnings

Keep out of reach of children under 6 years of age.if you accidentally swallow more than used for brushing, seek professional help or contact a Poison Control Center immediately.

Directions

Adults and children 2 years & older:

- Brush teeth thoroughly after meals or at least twice a day or use as directed by a dentist.
- Do not swallow.
- Instruct children under 6 years of age in good brushing and rinsing habits (to minimize swallowing, use a pea-sized amount)
- Supervise children's brushing until good habits are established.

Children under 2 years:

- Consult a dentist or doctor

Inactive Ingredients

Sorbitol, Silica, Treated Water, Glycerin, PEG-32, Sodium Lauryl Sulfate, Flavor, Titanium Dioxide, Cellulose Gum, Carrageenan, Trisodium Phosphate, Sodium Saccharin, Sodium Benzoate, Tetrasodium Pyrophosphate, FD&C Blue #1